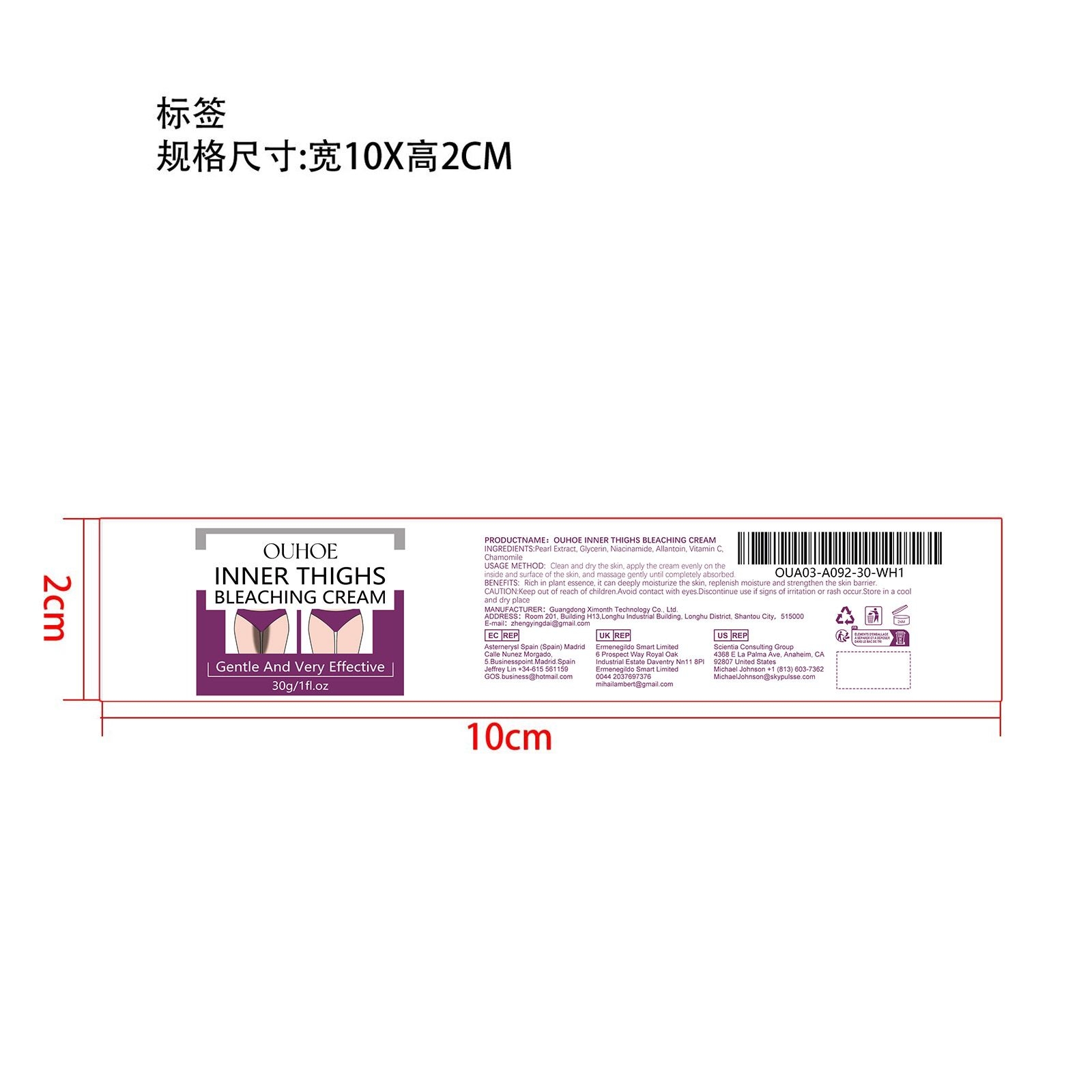 DRUG LABEL: OUHOE Inner Thighs Bleaching Cream
NDC: 84660-030 | Form: CREAM
Manufacturer: Guangdong Ximonth Technology Co., Ltd.
Category: otc | Type: HUMAN OTC DRUG LABEL
Date: 20240926

ACTIVE INGREDIENTS: ASCORBIC ACID 4.5 g/30 g; PEA 3 g/30 g; NIACINAMIDE 4.5 g/30 g; CHAMOMILE 3 g/30 g
INACTIVE INGREDIENTS: ALLANTOIN 9 g/30 g; GLYCERIN 6 g/30 g

Active Ingredient(s)

PEARL EXTRACT、NIACINAMIDE、VITAMIN C、CHAMOMILE

Purpose

Rich in plant essence, it can deeply moisturize the skin, replenish moisture and strengthen the skin barrier.

Use

Clean and dry the skin, apply the cream evenly on the inside and surface of the skin, and massage gently until completely absorbed.

Warnings

Please keep out of reach of children.Do not swallow.Please clean your hands before use to ensure the best results from the product.Discontinue use if signs of irritation or rash occur.Store in a cool and dry place.

Do not use

Discontinue use if signs of irritation or rash occur.

STOP USE

Discontinue use if signs of irritation or rash occur.

KEEP OUT OF REACH OF CHILDREN

Please keep out of reach of children. Do not swallow.

STORAGE AND HANDLING

Avoid freezing and excessive heat above 40C (104F) ）
Store in a cool and dry place.

INACTIVE INGREDIENT

GLYCERIN、ALLANTOIN